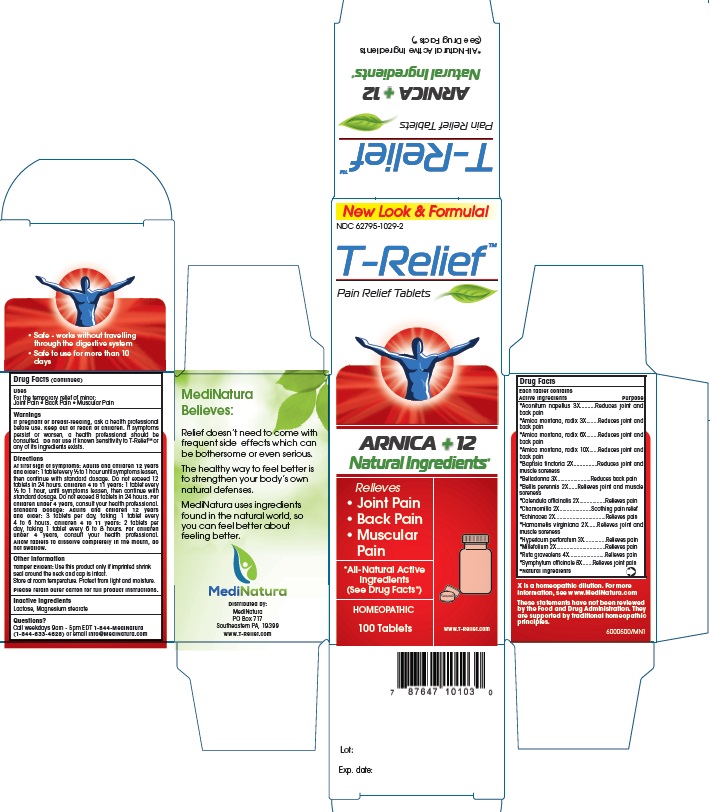 DRUG LABEL: T Relief
NDC: 62795-1029 | Form: TABLET
Manufacturer: MediNatura Inc
Category: homeopathic | Type: HUMAN OTC DRUG LABEL
Date: 20140925

ACTIVE INGREDIENTS: CALENDULA OFFICINALIS FLOWERING TOP 2 [hp_X]/1 1; HYPERICUM PERFORATUM 3 [hp_X]/1 1; BELLIS PERENNIS 2 [hp_X]/1 1; MATRICARIA RECUTITA 2 [hp_X]/1 1; ECHINACEA, UNSPECIFIED 2 [hp_X]/1 1; HAMAMELIS VIRGINIANA ROOT BARK/STEM BARK 2 [hp_X]/1 1; ACHILLEA MILLEFOLIUM 2 [hp_X]/1 1; BAPTISIA TINCTORIA ROOT 2 [hp_X]/1 1; ATROPA BELLADONNA 3 [hp_X]/1 1; RUTA GRAVEOLENS FLOWERING TOP 4 [hp_X]/1 1; COMFREY ROOT 8 [hp_X]/1 1; ACONITUM NAPELLUS 3 [hp_X]/1 1; ARNICA MONTANA 3 [hp_X]/1 1
INACTIVE INGREDIENTS: MAGNESIUM STEARATE 1 kg/1 1; LACTOSE 1 kg/1 1

T Relief Tablet

ACTIVE INGREDIENTS

*Aconitum napellus 3X, *Arnica montana, radix 3X, *Arnica montana, radix 6X, *Arnica montana, radix 10X, *Baptisia tinctoria 2X, *Belladonna 3X, *Bellis perennis 2X, *Calendula officinalis 2X, *Chamomilla 2X, *Echinacea 2X, *Hamamelis virginiana 2X, *Hypericum perforatum 3X, *Millefolium 2X, *Ruta graveolens 4X, *Symphytum officinale 8X

*Natural Ingredients

INACTIVE INGREDIENTS

Lactose Magnesium stearate

Indications

Relieves

- joint pain
- back pain
- muscular pain

KEEP OUT OF REACH OF CHILDREN

PURPOSE

For the temporary relief of minor: Joint pain, Back pain, Muscular pain

WARNINGS

If pregnant or breast-feeding, ask a health professional before use. Keep out of reach of children. If symptoms persist or worsen, a health professional shoul be consulted. Do not use if known sensitivity to T-Relief™ or any of its ingredients exists.

DOSAGE AND ADMINISTRATION

Adults and children 12 years and older: 1 tablet every 1/2 to 1 hour until symptoms lessen, then continue with standard dose. Do not exceed 12 tablets in 24 hours. Children 4 to 11 years: 1 tablet every 1/2 to 1 hour, until symptoms lessen, then continue with standard dosage. Do not exceed 8 tablets in 24 hours. Standard Dosage: Adults and children 12 years and older: 3 tablets per day, taking 1 tablet every 4 to 6 hours. Children 4 to 11 years: 2 tablets per day, taking 1 tablet every 6 to 8 hours. For children under 4 years, consult your health professional. Allow tablets to dissolve completely in the mouth, do not swallow.